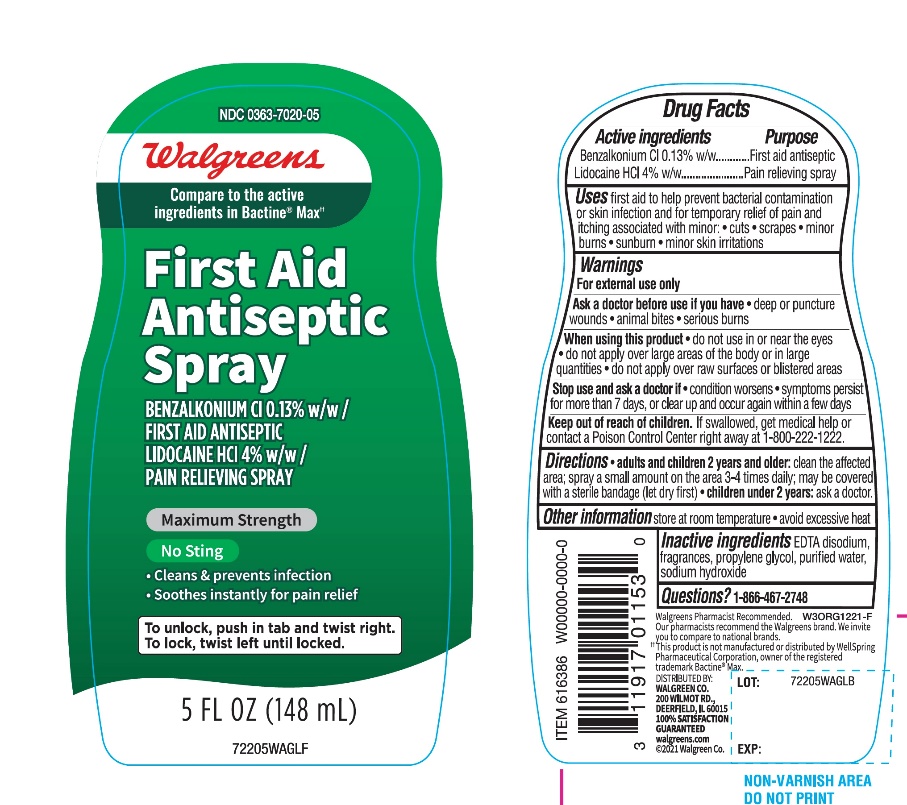 DRUG LABEL: Walgreen Maximum strength

NDC: 0363-7020 | Form: LIQUID
Manufacturer: WALGREENS CO.
Category: otc | Type: HUMAN OTC DRUG LABEL
Date: 20251126

ACTIVE INGREDIENTS: BENZALKONIUM CHLORIDE 0.13 g/100 mL; LIDOCAINE HYDROCHLORIDE 4 g/100 mL
INACTIVE INGREDIENTS: EDETATE DISODIUM; PROPYLENE GLYCOL; WATER; SODIUM HYDROXIDE

Walgreen Maximum Pain Relieving Cleansing Spray

Drug Facts

ACTIVE INGREDIENT

Active ingredients | Purpose
Benzalkonium Cl 0.13% w/w | First aid antiseptic
Lidocaine HCl 4% w/w | Pain relieving spray

Uses

first aid to help prevent bacterial contamination or skin infection, and for temporary relief of pain and itching associated with minor:

- cuts
- scrapes
- minor burns
- sunburn
- minor skin irritations

Warnings

For external use only

Ask a doctor before use if you have

- deep or puncture wounds
- animal bites
- serious burns

When using this product

- do not use in or near the eyes
- do not apply over large areas of the body or in large quantities
- do not apply over raw surfaces or blistered areas

Stop use and ask a doctor if

- condition worsens
- symptoms persist for more than 7 days, or clear up and occur again within a few days

Keep out of reach of children.If swallowed, get medical help or contact a Poison Control Center right away at 1-800-222-1222.

Directions

- adults and children 2 years and older:clean the affected area; apply a small amount on the area 3-4 times daily; may be covered with a sterile bandage (let dry first)
- children under 2 years:ask a doctor

Other information

- store at room temperature
- avoid excessive heat

Inactive ingredients

EDTA disodium, fragrances, propylene glycol, purified water, sodium hydroxide

Questions?

1-866-467-2748

Principal Display Package Label Panel

Compare to the active ingredients in Bectine®Max*

NDC# 0363-7020-05

Maximum Strength

PAIN RELIEVING

Cleansing Spray

First Aid Antiseptic & Pain Reliever

MAX STRENGTH GERM KILLING

4% Lidocaine HCl

MAX STRENGTH PAIN RELIEVER

NO STING

*germs commonly associated with skin infection.

To unlock, push in tab and twist right.

To lock, twist left until locked

5 FL OZ (148 mL)

*This product is not manufactured or distributed by WellSpring Pharmaceuticals Corporation, owner of the registered trademark Bectine® Max.

Distributed By: